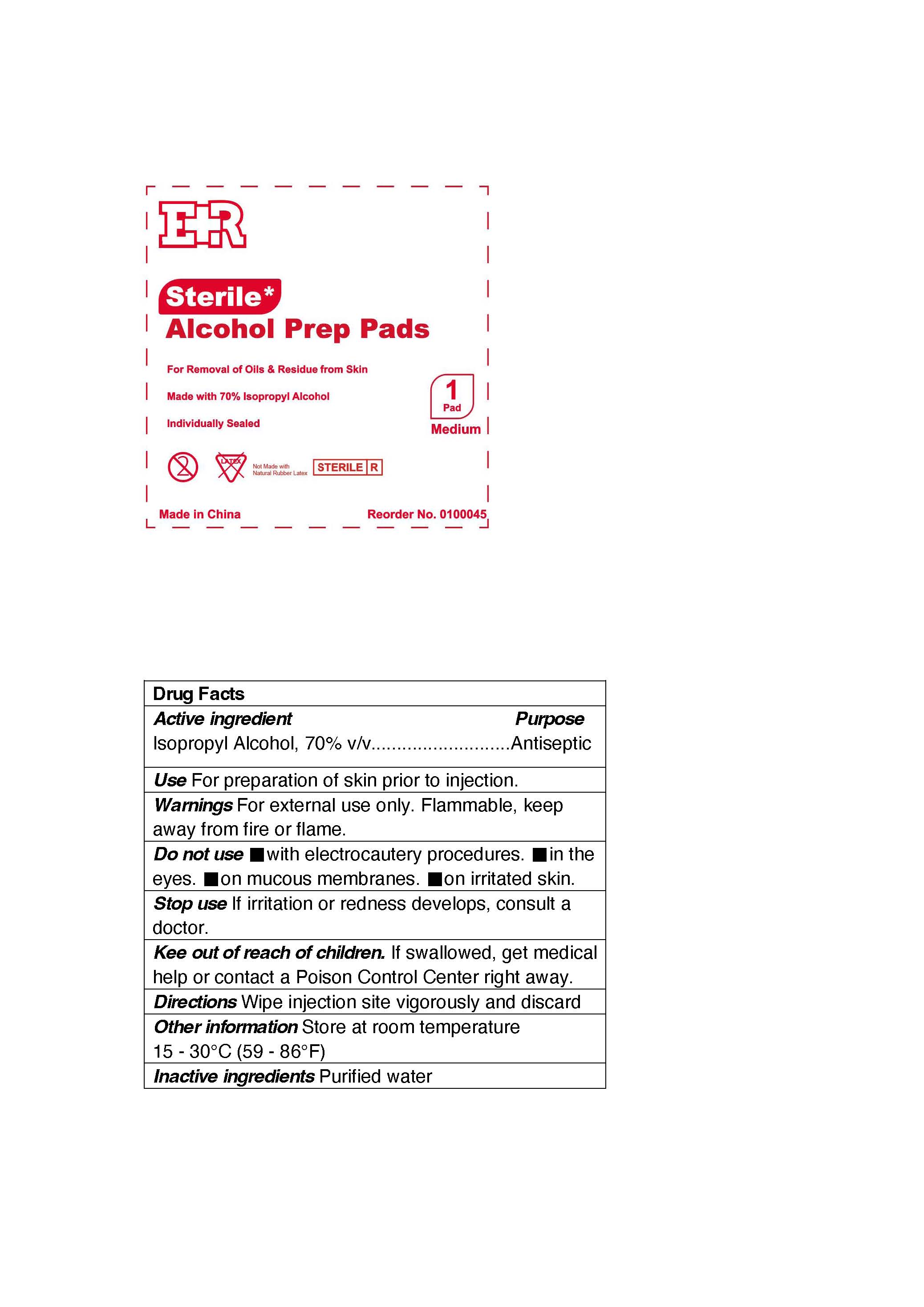 DRUG LABEL: ER Alcohol Prep
NDC: 72976-012 | Form: PATCH
Manufacturer: EVER READY FIRST AID
Category: otc | Type: HUMAN OTC DRUG LABEL
Date: 20230602

ACTIVE INGREDIENTS: ISOPROPYL ALCOHOL 70 g/100 g
INACTIVE INGREDIENTS: WATER

ER Alcohol Prep Pad

Active ingredient

Isopropyl Alcohol 70% v/v

Purpose

Antiseptic

Use

For preparation of skin prior to injection.

Warnings

For external use only. Flammable, keep away from fire or flame.

Do not use

■with electrocautery procedures.

■in the eyes.

■on mucous membranes.

■on irritated skin.

Stop use

If irritation or redness develops, consult a doctor.

Kee out of reach of children.

If swallowed, get medical help or contact a Poison Control Center right away.

Directions

Wipe injection site vigorously and discard

Other information

Store at room temperature15 - 30°C (59 - 86°F)

Inactive ingredients

Purified water.